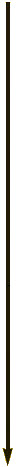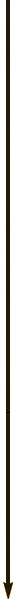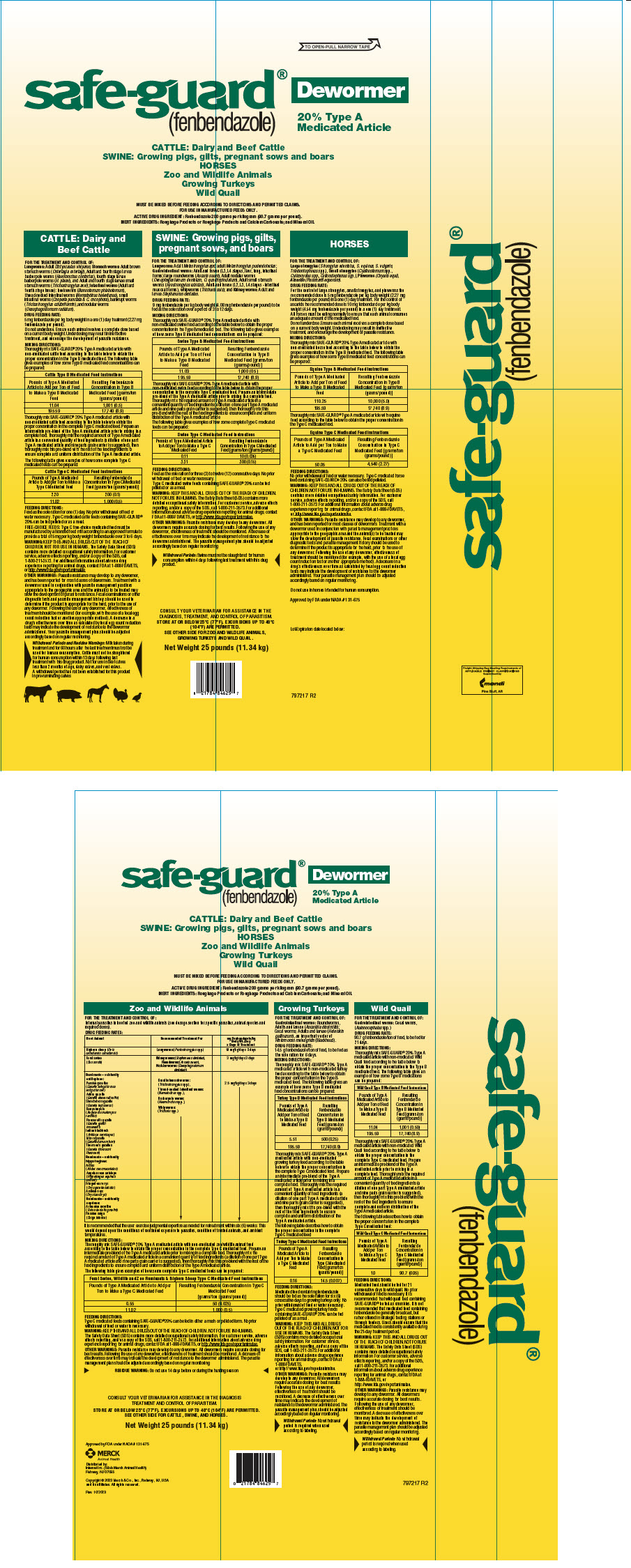 DRUG LABEL: Safe-Guard
NDC: 57926-090 | Form: POWDER
Manufacturer: Merck Sharp & Dohme Corp.
Category: animal | Type: OTC ANIMAL DRUG LABEL
Date: 20241119

ACTIVE INGREDIENTS: FENBENDAZOLE 200 g/1 kg

Safe-guard®
(fenbendazole)
Dewormer
20% Type A Medicated Article

CATTLE: Dairy and Beef Cattle

SWINE: Growing pigs, gilts, pregnant sows and boars

HORSES

Zoo and Wildlife Animals

Growing Turkeys

Wild Quail

MUST BE MIXED BEFORE FEEDING ACCORDING TO DIRECTIONS AND PERMITTED CLAIMS.
FOR USE IN MANUFACTURED FEEDS ONLY.

ACTIVE DRUG INGREDIENT: Fenbendazole 200 grams per kilogram (90.7 grams per pound).

INERT INGREDIENTS: Roughage Products or Roughage Products and Calcium Carbonate; and Mineral Oil.

VETERINARY INDICATIONS

CATTLE: Dairy and Beef Cattle

FOR THE TREATMENT AND CONTROL OF:

Lungworms: Adult Dictyocaulus viviparus; Stomach worms: Adult brown stomach worms (Ostertagia ostertagi), Adult and fourth stage larvae barberpole worms (Haemonchus contortus), fourth stage larvae barberpole worms (H. placei), and Adult and fourth stage larvae small stomach worms (Trichostrongylus axei); Intestinal worms (Adult and fourth stage larvae): hookworms (Bunostomum phlebotomum), thread-necked intestinal worms (Nematodirus helvetianus), small intestinal worms (Cooperia punctata & C. oncophora), bankrupt worms (Trichostrongylus colubriformis), and nodular worms (Oesophagostomum radiatum).

DRUG FEEDING RATE:

5 mg fenbendazole per kg body weight in a one (1) day treatment (2.27 mg fenbendazole per pound).

Do not underdose. Ensure each animal receives a complete dose based on a current body weight. Underdosing may result in ineffective treatment, and encourage the development of parasite resistance.

MIXING DIRECTIONS:

Thoroughly mix SAFE-GUARD® 20% Type A medicated article with non-medicated cattle feed according to the table below to obtain the proper concentration in the Type B medicated feed. The following table gives examples of how some Type B medicated feed concentrations can be prepared:

Cattle Type B Medicated Feed Instructions
Pounds of Type A Medicated Article to Add per Ton of Feed to Make a Type B Medicated Feed | Resulting Fenbendazole Concentration in Type B Medicated Feed [grams/ton (grams/pound)]
11.04 | 1,001 (0.5)
195.59 | 17,740 (8.9)

Thoroughly mix SAFE-GUARD® 20% Type A medicated article with non-medicated cattle feed according to the table below to obtain the proper concentration in the complete Type C medicated feed. Prepare an intermediate pre-blend of the Type A medicated article prior to mixing in a complete feed. Thoroughly mix the required amount of Type A medicated article in a convenient quantity of feed ingredients (a dilution of one part Type A medicated article and nine parts grain carrier is suggested), then thoroughly mix this pre-blend with the rest of the feed ingredients to ensure complete and uniform distribution of the Type A medicated article.

The following table gives examples of how some complete Type C medicated feeds can be prepared:

Cattle Type C Medicated Feed Instructions
Pounds of Type A Medicated Article to Add per Ton to Make a Type C Medicated Feed | Resulting Fenbendazole Concentration in Type C Medicated Feed [grams/ton (grams/pound)]
2.20 | 200 (0.1)
11.02 | 1,000 (0.5)

FEEDING DIRECTIONS:

Feed as the sole ration for one (1) day. No prior withdrawal of feed or water necessary. Type C medicated cattle feeds containing SAFE-GUARD® 20% can be fed pelleted or as a meal.

FREE-CHOICE FEEDS: Type C free-choice medicated feed must be manufactured by a licensed feed mill according to an approved formula to provide a total of 5 mg per kg body weight fenbendazole over 3 to 6 days.

WARNINGS

WARNING: KEEP THIS AND ALL DRUGS OUT OF THE REACH OF CHILDREN. NOT FOR USE IN HUMANS. The Safety Data Sheet (SDS) contains more detailed occupational safety information. For customer service, adverse effects reporting, and/or a copy of the SDS, call 1-800-211-3573. For additional information about adverse drug experience reporting for animal drugs, contact FDA at 1-888-FDAVETS, or http://www.fda.gov/reportanimalae.

OTHER WARNINGS: Parasite resistance may develop to any dewormer, and has been reported for most classes of dewormers. Treatment with a dewormer used in conjunction with parasite management practices appropriate to the geographic area and the animal(s) to be treated may slow the development of parasite resistance. Fecal examinations or other diagnostic tests and parasite management history should be used to determine if the product is appropriate for the herd, prior to the use of any dewormer. Following the use of any dewormer, effectiveness of treatment should be monitored (for example, with the use of a fecal egg count reduction test or another appropriate method). A decrease in a drug's effectiveness over time as calculated by fecal egg count reduction tests may indicate the development of resistance to the dewormer administered. Your parasite management plan should be adjusted accordingly based on regular monitoring.

RESIDUE WARNING

Withdrawal Periods and Residue Warnings: Milk taken during treatment and for 60 hours after the last treatment must not be used for human consumption. Cattle must not be slaughtered for human consumption within 13 days following last treatment with this drug product. Not for use in beef calves less than 2 months of age, dairy calves, and veal calves. A withdrawal period has not been established for this product in pre-ruminating calves.

VETERINARY INDICATIONS

SWINE: Growing pigs, gilts, pregnant sows, and boars

FOR THE TREATMENT AND CONTROL OF:

Lungworms: Adult Metastrongylus apri, adult Metastrongylus pudendotectus; Gastrointestinal worms: Adult and larvae (L3, L4 stages, liver, lung, intestinal forms) large roundworms (Ascaris suum), Adult nodular worms (Oesophagostomum dentatum, O. quadrispinulatum), Adult small stomach worms (Hyostrongylus rubidus), Adult and larvae (L2, L3, L4 stages - intestinal mucosal forms), whipworms (Trichuris suis); and Kidney worms: Adult and larvae Stephanurus dentatus.

DRUG FEEDING RATE:

9 mg fenbendazole per kg body weight (4.08 mg fenbendazole per pound) to be fed as the sole ration over a period of 3 to 12 days.

MIXING DIRECTIONS:

Thoroughly mix SAFE-GUARD® 20% Type A medicated article with non-medicated swine feed according to the table below to obtain the proper concentration in the Type B medicated feed. The following table gives examples of how some Type B medicated feed concentrations can be prepared:

Swine Type B Medicated Feed Instructions
Pounds of Type A Medicated Article to Add per Ton of Feed to Make a Type B Medicated Feed | Resulting Fenbendazole Concentration in Type B Medicated Feed [grams/ton (grams/pound)]
11.03 | 1,000 (0.5)
195.59 | 17,740 (8.9)

Thoroughly mix SAFE-GUARD® 20% Type A medicated article with non-medicated swine feed according to the table below to obtain the proper concentration in the complete Type C medicated feed. Prepare an intermediate pre-blend of the Type A medicated article prior to mixing in a complete feed. Thoroughly mix the required amount of Type A medicated article in a convenient quantity of feed ingredients (a dilution of one part Type A medicated article and nine parts grain carrier is suggested), then thoroughly mix this pre-blend with the rest of the feed ingredients to ensure complete and uniform distribution of the Type A medicated article.

The following table gives examples of how some complete Type C medicated feeds can be prepared:

Swine Type C Medicated Feed Instructions
Pounds of Type A Medicated Article to Add per Ton to Make a Type C Medicated Feed | Resulting Fenbendazole Concentration in Type C Medicated Feed [grams/ton (grams/pound)]
0.11 | 10 (0.005)
3.31 | 300 (0.15)

FEEDING DIRECTIONS:

Feed as the sole ration for three (3) to twelve (12) consecutive days. No prior withdrawal of feed or water necessary.

Type C medicated swine feeds containing SAFE-GUARD® 20% can be fed pelleted or as a meal.

WARNINGS

WARNING: KEEP THIS AND ALL DRUGS OUT OF THE REACH OF CHILDREN. NOT FOR USE IN HUMANS. The Safety Data Sheet (SDS) contains more detailed occupational safety information. For customer service, adverse effects reporting, and/or a copy of the SDS, call 1-800-211-3573. For additional information about adverse drug experience reporting for animal drugs, contact FDA at 1-888-FDAVETS, or http://www.fda.gov/reportanimalae.

OTHER WARNINGS: Parasite resistance may develop to any dewormer. All dewormers require accurate dosing for best results. Following the use of any dewormer, effectiveness of treatment should be monitored. A decrease of effectiveness over time may indicate the development of resistance to the dewormer administered. The parasite management plan should be adjusted accordingly based on regular monitoring.

Withdrawal Periods: Swine must not be slaughtered for human consumption within 4 days following last treatment with this drug product.

HORSES

FOR THE TREATMENT AND CONTROL OF:

Large strongyles (Strongylus edentatus, S. equinus, S. vulgaris, Triodontophorus spp.), Small strongyles (Cyathostomum spp., Cylicocyclus spp., Cylicostephanus spp.), Pinworms (Oxyuris equi), Ascarids (Parascaris equorum).

DRUG FEEDING RATE:

For the control of large strongyles, small strongyles, and pinworms the recommended dose is 5 mg fenbendazole per kg body weight (2.27 mg fenbendazole per pound) in a one (1) day treatment. For the control of ascarids the recommended dose is 10 mg fenbendazole per kg body weight (4.54 mg fenbendazole per pound) in a one (1) day treatment.

All horses must be eating normally to ensure that each animal consumes an adequate amount of the medicated feed.

Do not underdose. Ensure each animal receives a complete dose based on a current body weight. Underdosing may result in ineffective treatment, and encourage the development of parasite resistance.

MIXING DIRECTIONS:

Thoroughly mix SAFE-GUARD® 20% Type A medicated article with non-medicated horse feed according to the table below to obtain the proper concentration in the Type B medicated feed. The following table gives examples of how some Type B medicated feed concentrations can be prepared:

Equine Type B Medicated Feed Instructions
Pounds of Type A Medicated Article to Add per Ton of Feed to Make a Type B Medicated Feed | Resulting Fenbendazole Concentration in Type B Medicated Feed [grams/ton (grams/pound)]
110.25 | 10,000 (5.0)
195.59 | 17,740 (8.9)

Thoroughly mix SAFE-GUARD® Type A medicated article with equine feed according to the table below to obtain the proper concentration in the Type C medicated feed.

Equine Type C Medicated Feed Instructions
Pounds of Type A Medicated Article to Add per Ton to Make a Type C Medicated Feed | Resulting Fenbendazole Concentration in Type C Medicated Feed [grams/ton (grams/pound)]
50.05 | 4,540 (2.27)

FEEDING DIRECTIONS:

No prior withdrawal of feed or water necessary. Type C medicated horse feed containing SAFE-GUARD® 20% can also be fed pelleted.

WARNINGS

WARNING: KEEP THIS AND ALL DRUGS OUT OF THE REACH OF CHILDREN. NOT FOR USE IN HUMANS. The Safety Data Sheet (SDS) contains more detailed occupational safety information. For customer service, adverse effects reporting, and/or a copy of the SDS, call 1-800-211-3573. For additional information about adverse drug experience reporting for animal drugs, contact FDA at 1-888-FDAVETS, or http://www.fda.gov/reportanimalae.

RESIDUE WARNING

OTHER WARNINGS: Parasite resistance may develop to any dewormer, and has been reported for most classes of dewormers. Treatment with a dewormer used in conjunction with parasite management practices appropriate to the geographic area and the animal(s) to be treated may slow the development of parasite resistance. Fecal examinations or other diagnostic tests and parasite management history should be used to determine if the product is appropriate for the herd, prior to the use of any dewormer. Following the use of any dewormer, effectiveness of treatment should be monitored (for example, with the use of a fecal egg count reduction test or another appropriate method). A decrease in a drug's effectiveness over time as calculated by fecal egg count reduction tests may indicate the development of resistance to the dewormer administered. Your parasite management plan should be adjusted accordingly based on regular monitoring.

Do not use in horses intended for human consumption.

Approved by FDA under NADA # 131-675

CONSULT YOUR VETERINARIAN FOR ASSISTANCE IN THE DIAGNOSIS, TREATMENT, AND CONTROL OF PARASITISM.

STORAGE AND HANDLING

STORE AT OR BELOW 25°C (77°F). EXCURSIONS UP TO 40°C (104°F) ARE PERMITTED.

SEE OTHER SIDE FOR ZOO AND WILDLIFE ANIMALS, GROWING TURKEYS AND WILD QUAIL.

Net Weight 25 pounds (11.34 kg)

Lot/Expiration date located below:

797217 R2

Zoo and Wildlife Animals

FOR THE TREATMENT AND CONTROL OF:

Internal parasites in hoofed zoo and wildlife animals (see dosage section for specific parasites, animal species and required doses).

DRUG FEEDING RATES:

Host Animal | Recommended Treatment For | mg Fenbendazole/kg Body Wt./Day × Days of Treatment
Bighorn sheep (Ovis canadensis canadensis) | Lungworms: (Protostrongylus spp.) | 10 mg/kg/day × 3 days
Feral swine (Sus scrofa) | Kidney worms: (Stephanurus dentatus), Roundworms:(Ascaris suum), Nodular worms: (Oesophagostomum dentatum) | 3 mg/kg/day × 3 days
Ruminants – subfamily antilopinae: Persian gazelles (Gazella subgutturosa subgutturosa) Addra gazelle (Gazella dama ruficollis) Slendorhorn gazelle (Gazella leptoceros) Kenya impala (Aepyceros melampus rendilis) Roosevelt's gazelle (Gazella granti roosevelti) Indian blackbuck (Antilope cervicapra) Mhorr gazelle (Gazella dama mhorr) Thomson's gazelles (Gazella thomsoni thomsoni) Ruminants – subfamily hippotraginae: Addax (Addax nasomaculatus) Angolan roan antelope (Hippotragus equinus cottoni) Fringed-ear oryx (Oryx gazelle callotis) Arabian oryx (Oryx leucoryx) Ruminants – subfamily caprinae: Armenian mouflon (Ovis orientalis gmelini) Russian saiga (Saiga tatarica) | Small stomach worms: (Trichostrongylus spp.), Thread-necked intestinal worms: (Nematodirus spp.), Barberpole worms: (Haemonchus spp.), Whipworms: (Trichuris spp.) | 2.5 mg/kg/day × 3 days
Ruminants – subfamily antilopinae: Persian gazelles (Gazella subgutturosa subgutturosa) Addra gazelle (Gazella dama ruficollis) Slendorhorn gazelle (Gazella leptoceros) Kenya impala (Aepyceros melampus rendilis) Roosevelt's gazelle (Gazella granti roosevelti) Indian blackbuck (Antilope cervicapra) Mhorr gazelle (Gazella dama mhorr) Thomson's gazelles (Gazella thomsoni thomsoni) Ruminants – subfamily hippotraginae: Addax (Addax nasomaculatus) Angolan roan antelope (Hippotragus equinus cottoni) Fringed-ear oryx (Oryx gazelle callotis) Arabian oryx (Oryx leucoryx) Ruminants – subfamily caprinae: Armenian mouflon (Ovis orientalis gmelini) Russian saiga (Saiga tatarica) |  | 2.5 mg/kg/day × 3 days

It is recommended that the user exercise judgmental expertise as needed for retreatment within six (6) weeks. This would depend upon the conditions of continued exposure to parasites, condition of treated animals, and ambient temperatures.

MIXING DIRECTIONS:

Thoroughly mix SAFE-GUARD® 20% Type A medicated article with non-medicated zoo/wildlife animal feed according to the table below to obtain the proper concentration in the complete Type C medicated feed. Prepare an intermediate pre-blend of the Type A medicated article prior to mixing in a complete feed. Thoroughly mix the required amount of Type A medicated article in a convenient quantity of feed ingredients (a dilution of one part Type A medicated article and nine parts grain carrier is suggested), then thoroughly mix this pre-blend with the rest of the feed ingredients to ensure complete and uniform distribution of the Type A medicated article.

The following table gives examples of how some complete Type C medicated feeds can be prepared:

Feral Swine, Wildlife and Zoo Ruminants & Bighorn Sheep Type C Medicated Feed Instructions
Pounds of Type A Medicated Article to Add per Ton to Make a Type C Medicated Feed | Resulting Fenbendazole Concentration in Type C Medicated Feed [grams/ton (grams/pound)]
0.55 | 50 (0.025)
11.02 | 1,000 (0.5)

FEEDING DIRECTIONS:

Type C medicated feeds containing SAFE-GUARD® 20% can be fed in either a mash or pelleted form. No prior withdrawal of feed or water is necessary.

WARNINGS

WARNING: KEEP THIS AND ALL DRUGS OUT OF THE REACH OF CHILDREN. NOT FOR USE IN HUMANS. The Safety Data Sheet (SDS) contains more detailed occupational safety information. For customer service, adverse effects reporting, and/or a copy of the SDS, call 1-800-211-3573. For additional information about adverse drug experience reporting for animal drugs, contact FDA at 1-888-FDAVETS, or http://www.fda.gov/reportanimalae.

OTHER WARNINGS: Parasite resistance may develop to any dewormer. All dewormers require accurate dosing for best results. Following the use of any dewormer, effectiveness of treatment should be monitored. A decrease of effectiveness over time may indicate the development of resistance to the dewormer administered. The parasite management plan should be adjusted accordingly based on regular monitoring.

RESIDUE WARNING

RESIDUE WARNING: Do not use 14 days before or during the hunting season.

Growing Turkeys

FOR THE TREATMENT AND CONTROL OF:

Gastrointestinal worms: Roundworms, Adults and larvae (Ascaridia dissimilis); Cecal worms, Adults and larvae (Heterakis gallinarum), an important vector of Histomonas meleagridis (Blackhead).

DRUG FEEDING RATE:

14.5 g fenbendazole/ton of feed, to be fed as the sole ration for 6 days.

MIXING DIRECTIONS:

Thoroughly mix SAFE-GUARD® 20% Type A medicated article with non-medicated turkey feed according to the table below to obtain the proper concentration in the Type B medicated feed. The following table gives an example of how some Type B medicated feed concentrations can be prepared:

Turkey Type B Medicated Feed Instructions
Pounds of Type A Medicated Article to Add per Ton of Feed to Make a Type B Medicated Feed | Resulting Fenbendazole Concentration in Type B Medicated Feed [grams/ton (grams/pound)]
5.51 | 500 (0.25)
195.59 | 17,740 (8.9)

Thoroughly mix SAFE-GUARD® 20% Type A medicated article with non-medicated growing turkey feed according to the table below to obtain the proper concentration in the complete Type C medicated feed. Prepare an intermediate pre-blend of the Type A medicated article prior to mixing in a complete feed. Thoroughly mix the required amount of Type A medicated article in a convenient quantity of feed ingredients (a dilution of one part Type A medicated article and nine parts grain carrier is suggested), then thoroughly mix this pre-blend with the rest of the feed ingredients to ensure complete and uniform distribution of the Type A medicated article.

The following table describes how to obtain the proper concentration in the complete Type C medicated feed:

Turkey Type C Medicated Feed Instructions
Pounds of Type A Medicated Article to Add per Ton to Make a Type C Medicated Feed | Resulting Fenbendazole Concentration in Type C Medicated Feed [grams/ton (grams/pound)]
0.16 | 14.5 (0.007)

FEEDING DIRECTIONS:

Medicated feed containing fenbendazole should be fed as the sole ration for six (6) consecutive days to growing turkeys only. No prior withdrawal of feed or water necessary. Type C medicated growing turkey feeds containing SAFE-GUARD® 20% can be fed pelleted or as a meal.

WARNINGS

WARNING: KEEP THIS AND ALL DRUGS OUT OF THE REACH OF CHILDREN. NOT FOR USE IN HUMANS. The Safety Data Sheet (SDS) contains more detailed occupational safety information. For customer service, adverse effects reporting, and/or a copy of the SDS, call 1-800-211-3573. For additional information about adverse drug experience reporting for animal drugs, contact FDA at 1-888-FDAVETS, or http://www.fda.gov/reportanimalae.

OTHER WARNINGS: Parasite resistance may develop to any dewormer. All dewormers require accurate dosing for best results. Following the use of any dewormer, effectiveness of treatment should be monitored. A decrease of effectiveness over time may indicate the development of resistance to the dewormer administered. The parasite management plan should be adjusted accordingly based on regular monitoring.

RESIDUE WARNING

Withdrawal Periods: No withdrawal period is required when used according to labeling.

Wild Quail

FOR THE TREATMENT AND CONTROL OF:

Gastrointestinal worms: Cecal worms, (Aulonocephalus spp.)

DRUG FEEDING RATE:

90.7 g fenbendazole/ton of feed, to be fed for 21 days.

MIXING DIRECTIONS:

Thoroughly mix SAFE-GUARD® 20% Type A medicated article with non-medicated Wild Quail feed according to the table below to obtain the proper concentration in the Type B medicated feed. The following table gives an example of how some Type B medications can be prepared:

Wild Quail Type B Medicated Feed Instructions
Pounds of Type A Medicated Article to Add per Ton of Feed to Make a Type B Medicated Feed | Resulting Fenbendazole Concentration in Type B Medicated Feed [grams/ton (grams/pound)]
11.04 | 1,001 (0.50)
195.59 | 17,740 (8.9)

Thoroughly mix SAFE-GUARD® 20% Type A medicated article with non-medicated Wild Quail feed according to the table below to obtain the proper concentration in the complete Type C medicated feed. Prepare an intermediate pre-blend of the Type A medicated article prior to mixing in a complete feed. Thoroughly mix the required amount of Type A medicated article in a convenient quantity of feed ingredients (a dilution of one part Type A medicated article and nine parts grain carrier is suggested), then thoroughly mix this pre-blend with the rest of the feed ingredients to ensure complete and uniform distribution of the Type A medicated article.

The following table describes how to obtain the proper concentration in the complete Type C medicated feed:

Wild Quail Type C Medicated Feed Instructions
Pounds of Type A Medicated Article to Add per Ton to Make a Type C Medicated Feed | Resulting Fenbendazole Concentration in Type C Medicated Feed [grams/ton (grams/pound)]
1.0 | 90.7 (0.05)

FEEDING DIRECTIONS:

Medicated feed should be fed for 21 consecutive days to wild quail. No prior withdrawal of feed is necessary. It is recommended that wild quail feed containing SAFE-GUARD® be fed as crumbles. It is not recommended that medicated feed containing fenbendazole be generally broadcast, but rather offered in strategic feeding stations or through feeders. Users should ensure that the medicated feed is consistently available during the 21-day treatment period.

WARNINGS

WARNING: KEEP THIS AND ALL DRUGS OUT OF THE REACH OF CHILDREN. NOT FOR USE IN HUMANS. The Safety Data Sheet (SDS) contains more detailed occupational safety information. For customer service, adverse effects reporting, and/or a copy of the SDS, call 1-800-211-3573. For additional information about adverse drug experience reporting for animal drugs, contact FDA at 1-888-FDAVETS, or http://www.fda.gov/reportanimalae.

OTHER WARNINGS: Parasite resistance may develop to any dewormer. All dewormers require accurate dosing for best results. Following the use of any dewormer, effectiveness of treatment should be monitored. A decrease of effectiveness over time may indicate the development of resistance to the dewormer administered. The parasite management plan should be adjusted accordingly based on regular monitoring.

RESIDUE WARNING

Withdrawal Periods: No withdrawal period is required when used according to labeling.

CONSULT YOUR VETERINARIAN FOR ASSISTANCE IN THE DIAGNOSIS TREATMENT AND CONTROL OF PARASITISM.

STORAGE AND HANDLING

STORE AT OR BELOW 25°C (77°F). EXCURSIONS UP TO 40°C (104°F) ARE PERMITTED.

SEE OTHER SIDE FOR CATTLE, SWINE, AND HORSES.

Net Weight 25 pounds (11.34 kg)

Approved by FDA under NADA # 131-675

MERCK
Animal Health

Distributed by:
Intervet Inc. (d/b/a Merck Animal Health)
Rahway, NJ 07065

Copyright © 2023 Merck & Co., Inc., Rahway, NJ, USA
and its affiliates. All rights reserved.

Rev. 10/2023

PRINCIPAL DISPLAY PANEL - 11.34 kg Bag Label

TO OPEN-PULL NARROW TAPE

safe-guard®
(fenbendazole)
Dewormer

20% Type A
Medicated Article

CATTLE: Dairy and Beef Cattle
SWINE: Growing pigs, gilts, pregnant sows and boars
HORSES
Zoo and Wildlife Animals
Growing Turkeys
Wild Quail

MUST BE MIXED BEFORE FEEDING ACCORDING TO DIRECTIONS AND PERMITTED CLAIMS.
FOR USE IN MANUFACTURED FEEDS ONLY.

ACTIVE DRUG INGREDIENT: Fenbendazole 200 grams per kilogram (90.7 grams per pound).
INERT INGREDIENTS: Roughage Products or Roughage Products and Calcium Carbonate; and Mineral Oil.